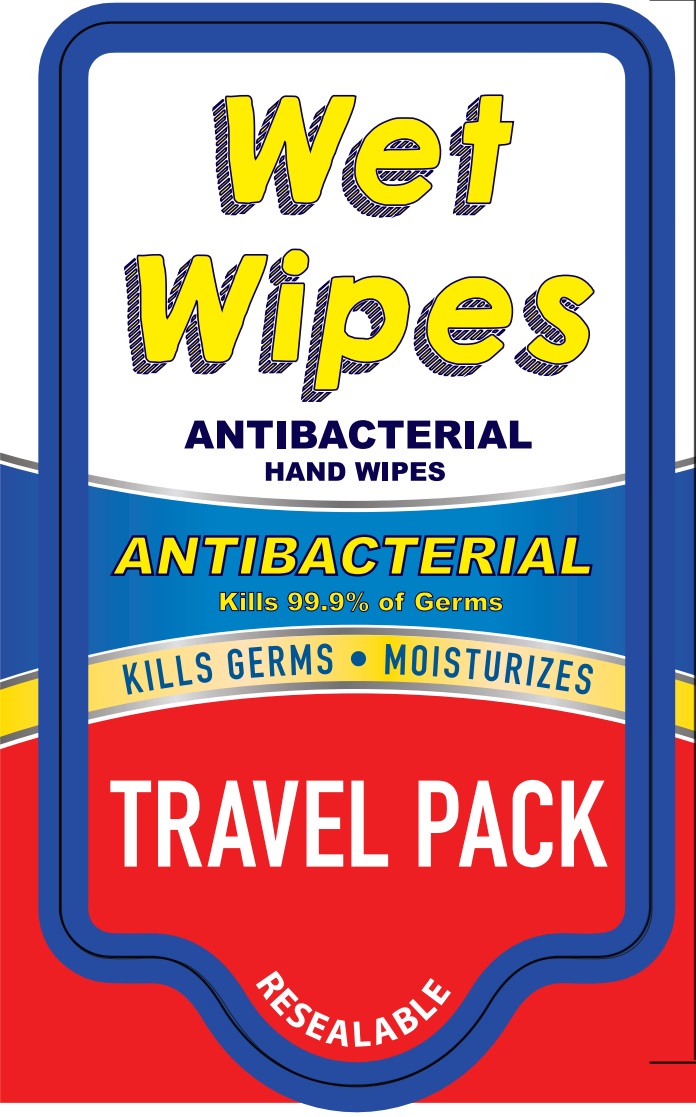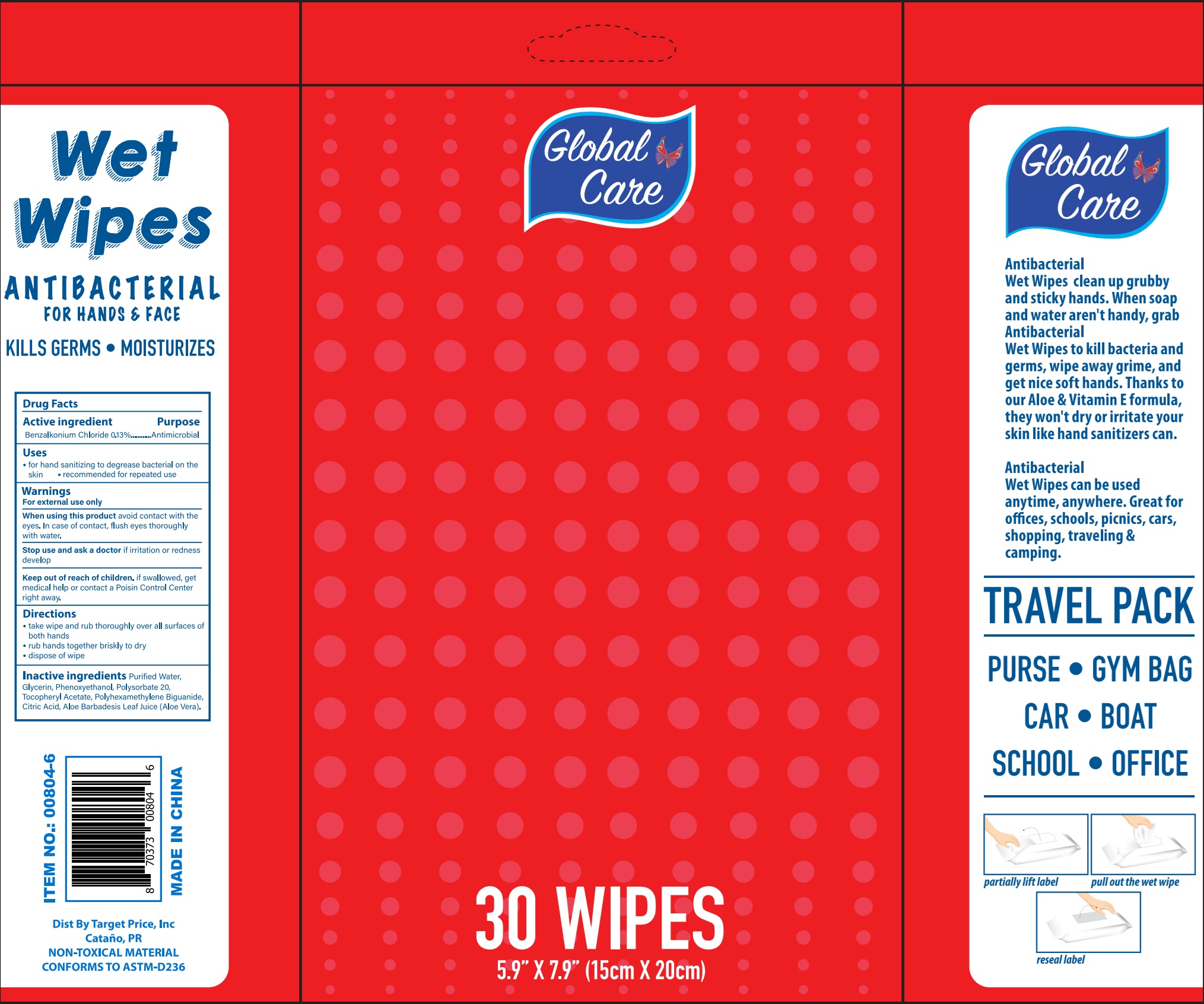 DRUG LABEL: Wet Wipes Antibacterial Hand Wipes, Travel Pack
NDC: 72146-037 | Form: CLOTH
Manufacturer: TARGET PRICE INC
Category: otc | Type: HUMAN OTC DRUG LABEL
Date: 20250808

ACTIVE INGREDIENTS: BENZETHONIUM CHLORIDE 1.3 mg/1 mL
INACTIVE INGREDIENTS: ALOE VERA LEAF; WATER; GLYCERIN; PHENOXYETHANOL; POLYSORBATE 20; POLIHEXANIDE; .ALPHA.-TOCOPHEROL ACETATE; CITRIC ACID MONOHYDRATE

Wet Wipes Antibacterial Hand Wipes, Travel Pack

Active Ingrdient

Benzethonium Chloride 0.13%

Purpose

Antimicrobial

Uses

- for hand sanitizing to decrease bacterial on skin
- recommended for repeated use

WARNINGS

For external use only

When using this product

avoid contact with the eyes. In case of contact, flush eyes thoroughly with water.

Stop use and ask a doctor if

irritation or redness develop

Keep out of reach of children.

if swallowed, get medical help or contact a Poisin Control Center right away.

Directions

- take wipe and rub thoroughly over all surfaces of both hands
- rub hands together briskly to dry
- dispose of wipe

Inactive Ingredients:

Purified Water, Glycerin, Phenoxyethanol, Polysorbate 20, Tocopheryl Acetate, Polyhexamethylene Biguanide, Citric Acid, Aloe Barbadesis Leaf Juice (Aloe Vera).